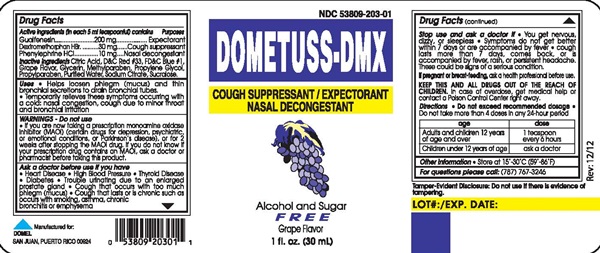 DRUG LABEL: DOMETUSS-DMX
NDC: 53809-203 | Form: LIQUID
Manufacturer: Domel Laboratories
Category: otc | Type: HUMAN OTC DRUG LABEL
Date: 20241205

ACTIVE INGREDIENTS: GUAIFENESIN 200 mg/5 mL; DEXTROMETHORPHAN HYDROBROMIDE 30 mg/5 mL; PHENYLEPHRINE HYDROCHLORIDE 10 mg/5 mL
INACTIVE INGREDIENTS: CITRIC ACID MONOHYDRATE; D&C RED NO. 33; FD&C BLUE NO. 1; GLYCERIN; METHYLPARABEN; PROPYLENE GLYCOL; PROPYLPARABEN; WATER; SODIUM CITRATE, UNSPECIFIED FORM; SUCRALOSE

DOMETUSS-DMX

Drug Facts Active ingredients (in each 5 mL teaspoonful) contains

Guaifenesin 200mg

Dextromethorphan HBr, USP 30 mg

Phenylephrine HCL, USP 10 mg

Purpose

Expectorant

Cough suppressant

Nasal decongestant

KEEP THIS AND ALL DRUGS OUT OF THE REACH OF CHILDREN.

In case of overdose, get medical help or contact a Poison Control Center right away.

Uses

- Helps loosen phlegm (mucus) and thin bronchial secretions to drain bronchial tubes
- Temporarily relieves these symptoms occuring with a cold: nasal congestion, cough due to minor throat and bronchial irritation

Warnings - Do not use

- If you are now taking a prescription monoamine oxidase inhibitor (MAOI) (certain drugs for depression, psychiatric or emotional conditions or Parkinson's disease), or for 2 weeks after stopping the MAOI drug; if you do not know if your prescription drug contains an MAOI, ask a doctor or pharmacist before taking this product.

Ask a doctor before use if you have

- Heart Disease
- High Blood Pressure
- Thyroid Disease
- Diabetes
- Trouble urinating due to an enlarged prostate gland
- Cough that occurs with too much phlegm (mucus)
- Cough that lasts or is chronic such as bronchitis or emphysema

If pregnant or breast-feeding

as a health professional before use.

Stop use and ask a doctor if

- You get nervous, dizzy, or sleepless
- Symptoms do not get better within 7 days or are accompanied by a fever
- cough lasts more than 7 days, comes back, or is accompanied by fever, rash, or persistant headache.

These could be signs of a serious condition.

Directions

Do not exceed recommended dosage

Do not take more than 4 doses in any 24-hour period

age | dose
Adults and children 12 years of age and older | 1 teaspoon every 6 hours
Children under 12 years of age | ask a doctor

Inactive ingredients

Artificial grape flavor, citric acid, D&C red #33, FD&C blue #1, glycerin, methyl paraben, propylene glycol, propyl paraben, purified water, sodium citrate, sucralose.

Other information

• Store at 15°-30° C (59°-86°F)

Questions or comments?

Please call (787) 767-3246

DOMETUSS-DMX product label

NDC 53809-203-01

DOMETUSS-DMX

COUGH SUPPRESSANT/EXPECTORANT/NASAL DECONGESTANT

Alcohol and Sugar

FREE

Grape Flavor

1 Fl. Oz. (30 mL)

Rev: 12/12

Tamper-Evident Disclosure: Do not use if there is evidence of tampering.

LOT#:/EXP.DATE:

Manufactured for:

DOMEL

SAN JUAN, PUERTO RICO 00924